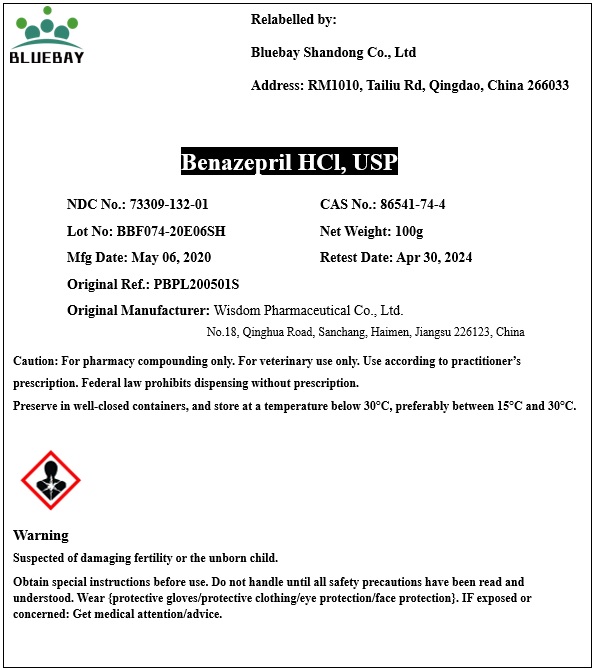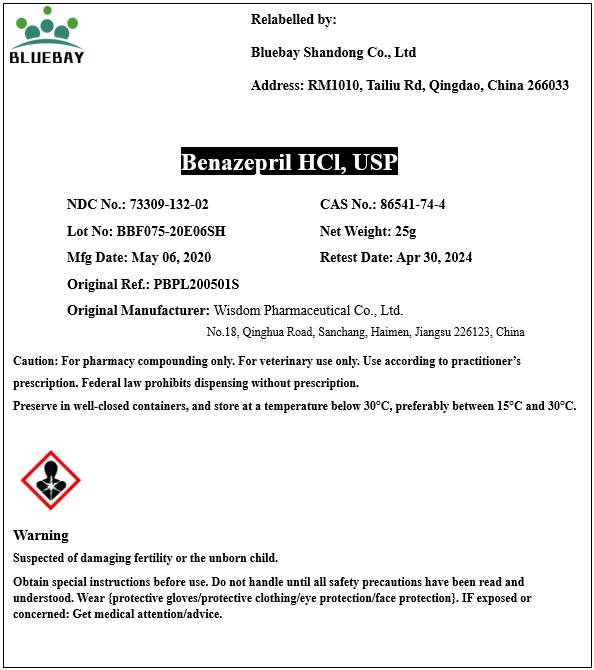 DRUG LABEL: Benazepril HCl
NDC: 73309-132 | Form: POWDER
Manufacturer: BLUEBAY SHANDONG CO.,LTD
Category: other | Type: BULK INGREDIENT
Date: 20200521

ACTIVE INGREDIENTS: BENAZEPRIL HYDROCHLORIDE 1 g/1 g

Benazepril HCl